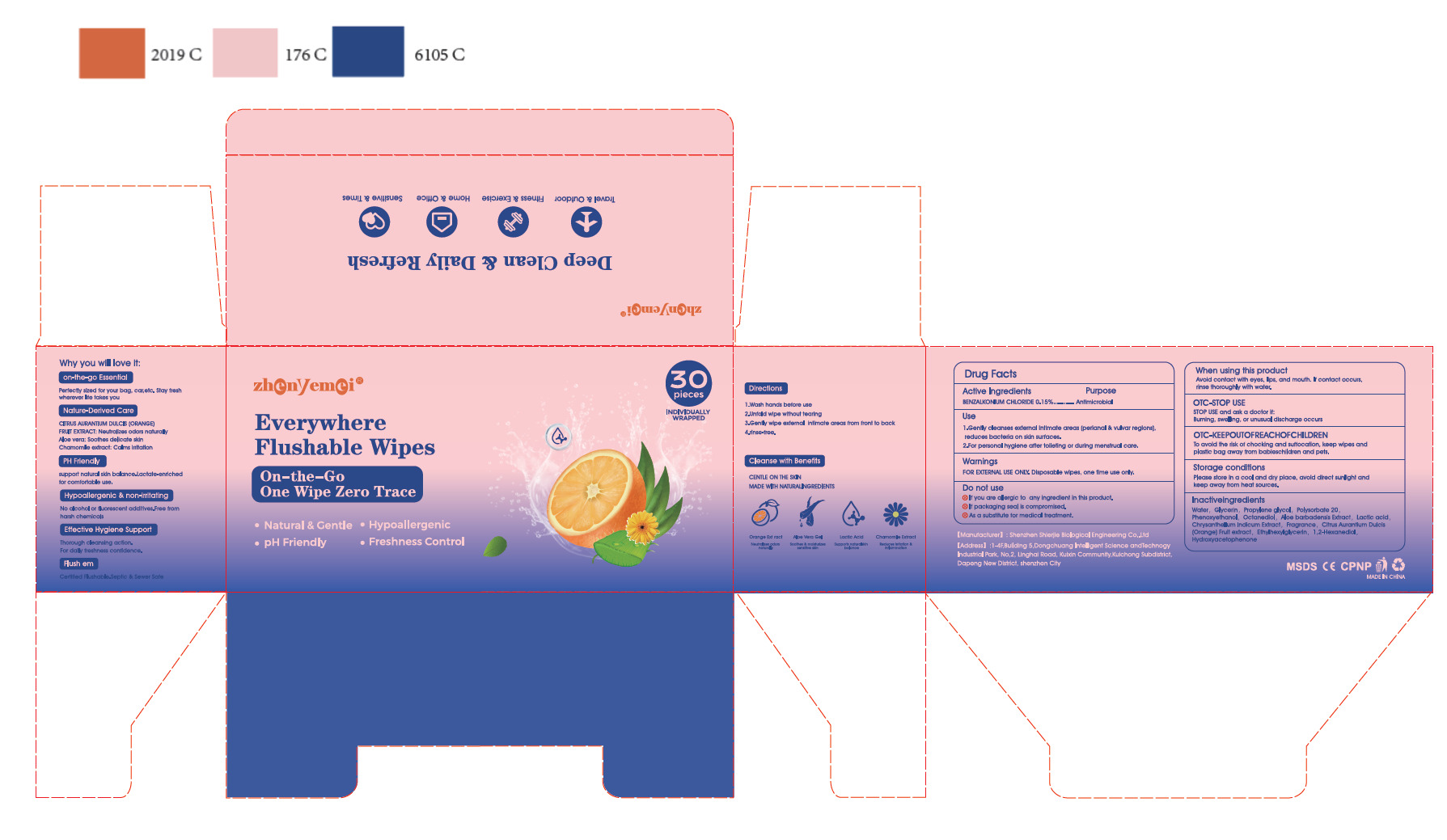 DRUG LABEL: Everywhere Flushable Wipes
NDC: 43116-042 | Form: CLOTH
Manufacturer: Shenzhen Shierjie Biological Engineering Co., LTD
Category: otc | Type: HUMAN OTC DRUG LABEL
Date: 20250608

ACTIVE INGREDIENTS: BENZALKONIUM CHLORIDE 0.15 U/100 U
INACTIVE INGREDIENTS: PHENOXYETHANOL; PROPYLENE GLYCOL; POLYSORBATE 20; OCTANEDIOL; WATER; GLYCERIN; ALOE BARBADENSIS LEAF; LACTIC ACID, L-; CHRYSANTHELLUM INDICUM TOP; CITRUS AURANTIUM DULCIS (ORANGE) FRUIT POWDER; ETHYLHEXYLGLYCERIN; 1,2-HEXANEDIOL; HYDROXYACETOPHENONE; CLOVE

43116-042

Active Ingredient

BENZALKONIUM CHLORIDE 0.15%

Purpose

Antimicrobial

Use

1 Gently cleanses external intimate areas (perianal & vulvar regions),
reduces bacteria on skin surfaces.
2.For personal hygiene after toileting or during menstrual care.

Warnings

FOR EXTERNAL USE ONLY. Disposable wipes, one time use only.

Do not use

1. If you are allergic to any ingredient in this product.
2. If packaging seal is compromised.
3. As a substitute for medical treatment.

When Using

Avoid contact with eyes, lips, and mouth. If contact occurs,
rinse thoroughly with water.

Stop Use

STOP USE and ask a doctor if:
Burning, swelling, or unusual discharge occurs

Keep Oot Of Reach Of Children

To avoid the risk of chocking and suffocation, keep wipes and
plastic bag away from babieschildren and pets.

Directions

1.Wash hands before use
2.Unfold wipe without tearing
3.Gently wipe external intimate areas from front to back
4.rinse-free.

Other information

Not have

Inactive ingredients

Water, Glycerin, Propylene glycol, Polysorbate 20，
Phenoxyethanol, Octanediol, Aloe barbadensis Extract, Lactic acid，
Chrysanthellum Indicum Extract, Fragrance, Citrus Aurantium Dulcis
(Orange) Fruit extract, Ethylhexylglycerin, 1 ,2-Hexanediol,
Hydroxyacetophenone